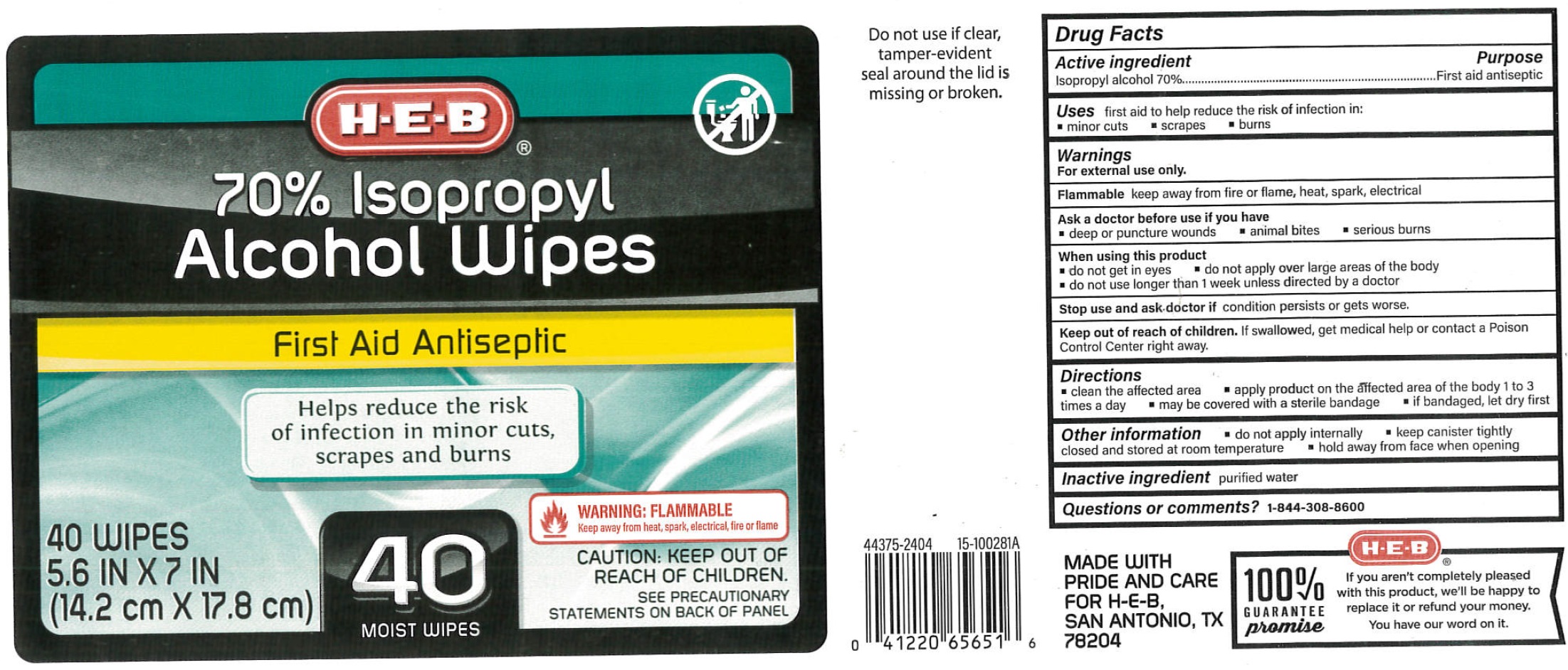 DRUG LABEL: HEB 70 Isopropyl Alcohol Wipes
NDC: 37808-356 | Form: CLOTH
Manufacturer: HEB Grocery Company
Category: otc | Type: HUMAN OTC DRUG LABEL
Date: 20251230

ACTIVE INGREDIENTS: ISOPROPYL ALCOHOL 0.7 mL/1 mL
INACTIVE INGREDIENTS: WATER

HEB 70% Isopropyl Alcohol Wipes

Active ingredient

Isopropyl alcohol 70%

Purpose

First aid antiseptic

Use

first aid to help prevent the risk of infection in: minor cuts scrapes burns

Warnings

For external use only

keep away from fire or flame, heat, spark, electrical Flammable

Ask a doctor before use if you have

deep or puncture wounds, animal bites or serious burns

When using this product

do not get in eyes do not apply over large areas of the body do not use longer than 1 week unless directed by a doctor

Stop use and ask a doctor if

condition persists or gets worse

Keep out of reach of children.

If swallowed, get medical help or contact a Poison Control Center right away.

Directions

clean the affected area apply product on the affected area of the body 1 to 3 times a day may be covered with a sterile bandage if bandaged, let dry first

Other information

Do not apply internally. Keep canister tightly closed and at controlled room temperature. Hold away from face when opening.

Inactive ingredient

purified water